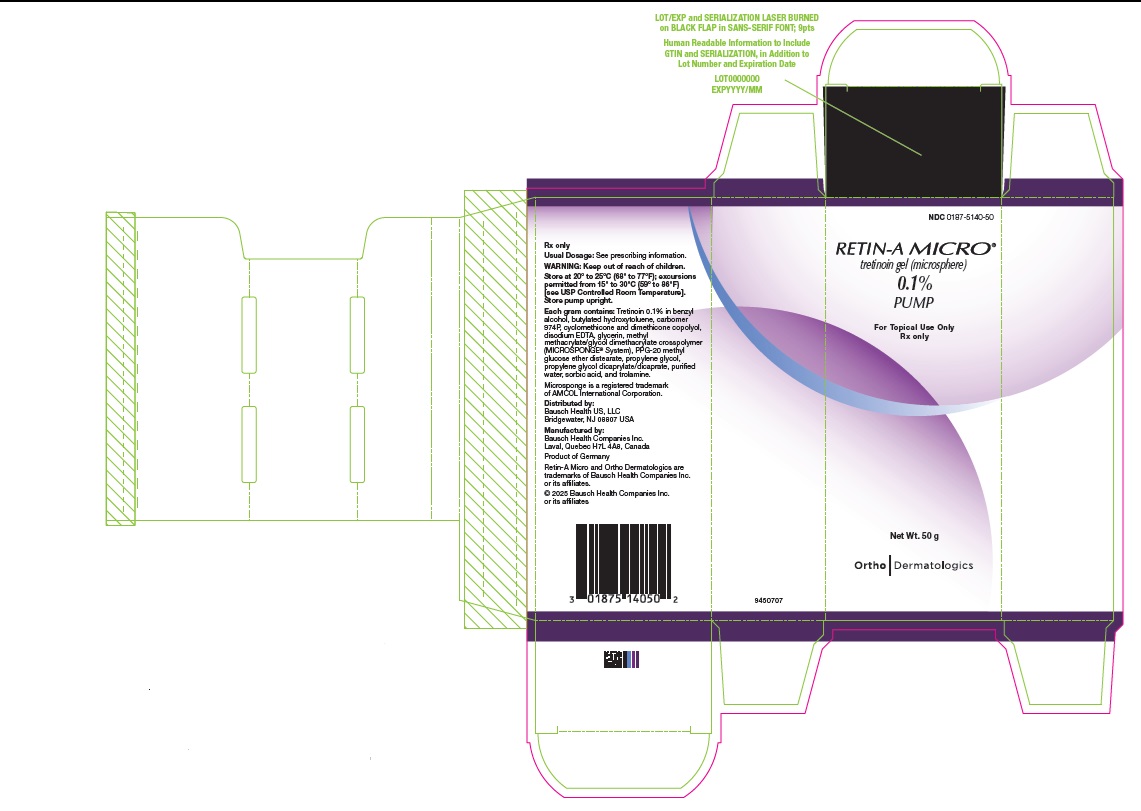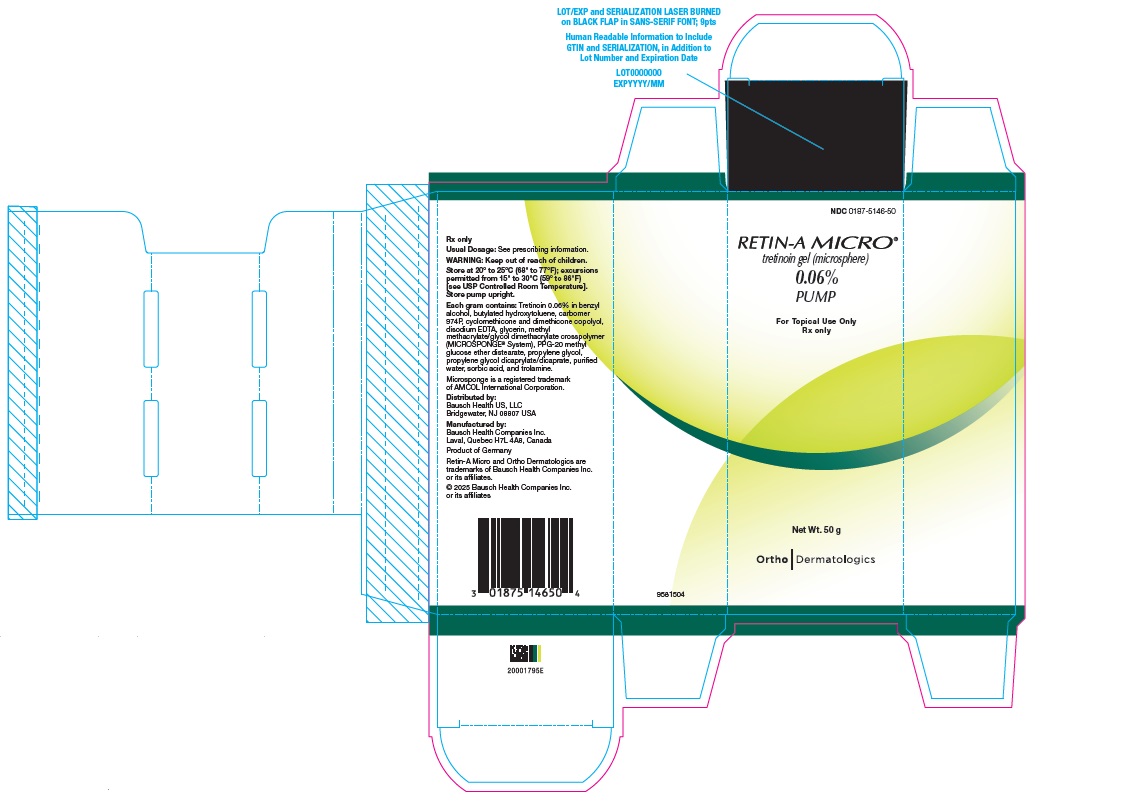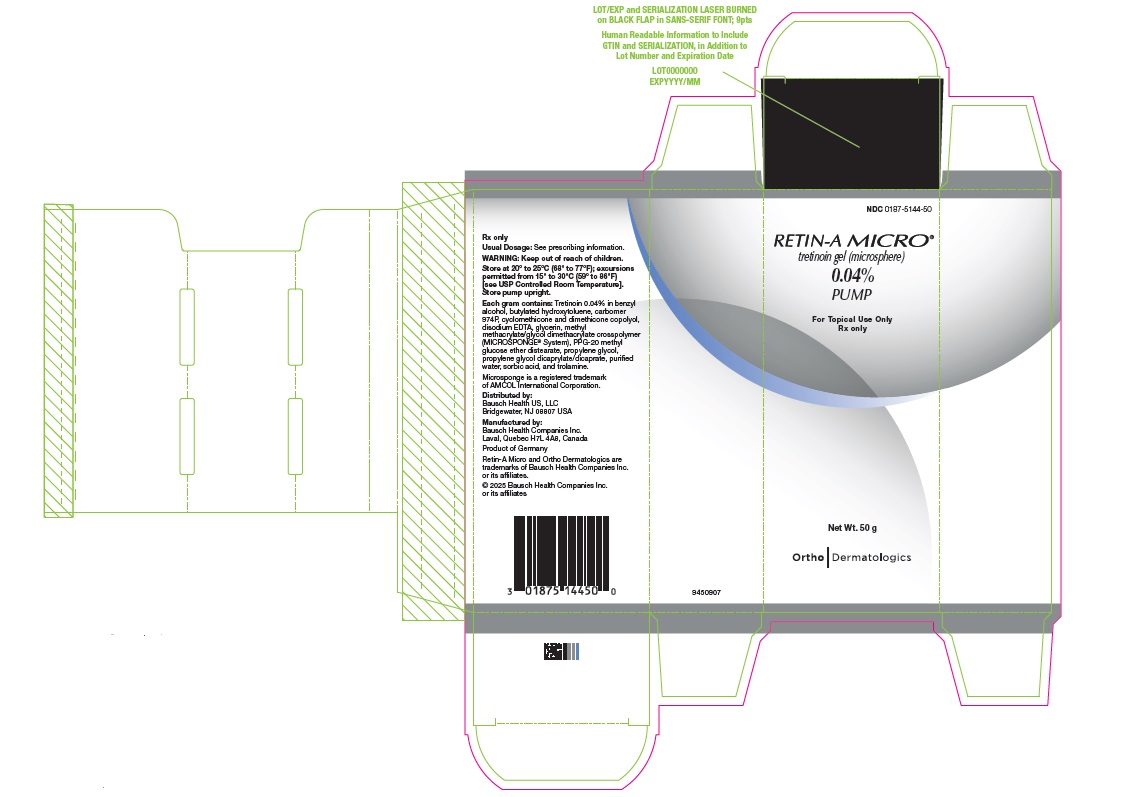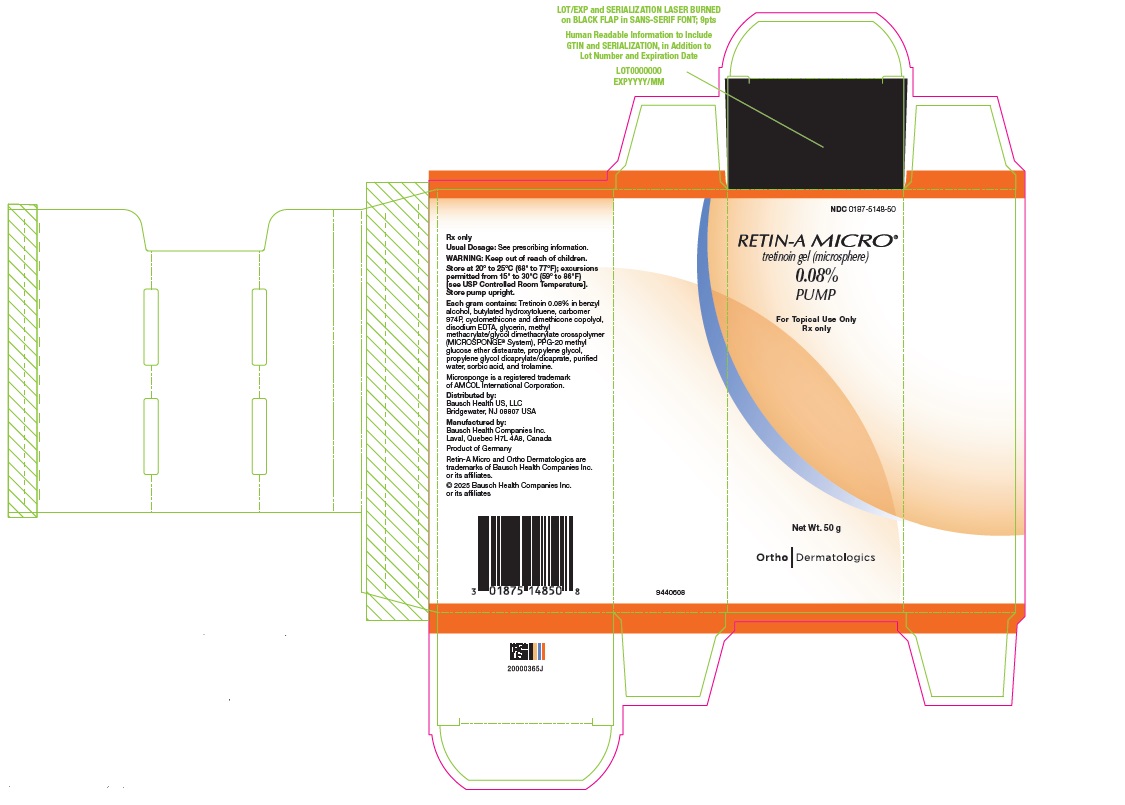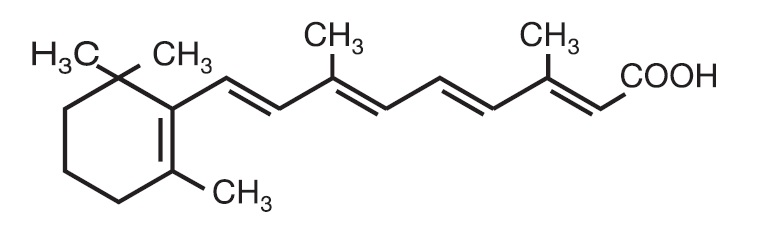 DRUG LABEL: Retin-A MICRO
NDC: 0187-5140 | Form: GEL
Manufacturer: Bausch Health US LLC
Category: prescription | Type: HUMAN PRESCRIPTION DRUG LABEL
Date: 20250901

ACTIVE INGREDIENTS: TRETINOIN 1 mg/1 g
INACTIVE INGREDIENTS: BENZYL ALCOHOL; BUTYLATED HYDROXYTOLUENE; CARBOMER HOMOPOLYMER TYPE B (ALLYL PENTAERYTHRITOL CROSSLINKED); EDETATE DISODIUM; GLYCERIN; PROPYLENE GLYCOL; WATER; SORBIC ACID; TROLAMINE

HIGHLIGHTS OF PRESCRIBING INFORMATION

These highlights do not include all the information needed to use RETIN-A MICRO safely and effectively. See full prescribing information for RETIN-A MICRO.
RETIN-A MICRO® (tretinoin) gel, for topical use
Initial U.S. Approval: 1971

1 INDICATIONS AND USAGE

RETIN-A MICRO is a retinoid indicated for the topical treatment of acne vulgaris in adults and pediatric patients 12 years of age and older. (1)

2 DOSAGE AND ADMINISTRATION

- For topical use only. Not for oral, ophthalmic, or intravaginal use. (2)
- Keep away from eyes, mouth, paranasal creases of the nose, and mucous membranes. (2)
- Apply a thin layer of RETIN-A MICRO to skin where acne lesions appear (cover the entire affected area) (0.04%, 0.06%, 0.08%, or 0.1%) once daily in the evening (2).

3 DOSAGE FORMS AND STRENGTHS

Gel: 0.04%, 0.06%, 0.08%, and 0.1% (3)

4 CONTRAINDICATIONS

None. (4)

5 WARNINGS AND PRECAUTIONS

- Local Skin Irritation: RETIN-A MICRO can cause local skin irritation, including excessive dryness, redness, swelling, peeling, itching, blistering, burning, or stinging (5.1)
- Avoid use on eczematous skin or during weather extremes, such as severe wind or cold.
- To reduce the risk of local skin irritation, wash the treated skin gently, using a mild, non-medicated soap, avoid washing the treated skin too often or scrubbing it hard when washing, and apply a topical moisturizer.
- If severe local skin irritation occurs, discontinue use temporarily or permanently.
- Initial Worsening of Inflammatory Acne Vulgaris: During the early weeks of RETIN-A MICRO treatment, an apparent exacerbation of inflammatory lesions may occur. If RETIN-A MICRO is tolerated, this should not be considered a reason to discontinue therapy. (5.2)
- Photosensitivity: RETIN-A MICRO can cause photosensitivity. Advise patients to avoid or minimize unnecessary exposure to UV light, including sunlight and sunlamps. Advise patients to use sunscreen (SPF ≥15) and sun-protective clothing if UV light exposure cannot be avoided. Avoid use on sunburn skin. (5.3)

6 ADVERSE REACTIONS

Most common adverse reactions were skin irritation, skin burning, erythema, peeling, dryness, itching, and dermatitis. (6.1)

To report SUSPECTED ADVERSE REACTIONS, contact Bausch Health US, LLC at 1-800-321-4576 or FDA at 1-800-FDA-1088 or www.fda.gov/medwatch.

FULL PRESCRIBING INFORMATION

1 INDICATIONS AND USAGE

RETIN-A MICRO® is indicated for the topical treatment of acne vulgaris in adults and pediatric patients 12 years of age and older.

2 DOSAGE AND ADMINISTRATION

For topical use only. Not for oral, ophthalmic, or intravaginal use.

- Prior to RETIN-A MICRO use, thoroughly cleanse area(s) with a mild, non-medicated cleanser then pat the skin dry.
- When applying RETIN-A MICRO, keep away from the eyes, the mouth, paranasal creases of the nose, and mucous membranes.
- Apply a thin layer of RETIN-A MICRO (0.04%, 0.06%, 0.08%, or 0.1%) to skin where acne lesions appear (cover the entire affected area), once daily in the evening. Do not apply more than a thin layer [see Warning and Precautions (5.1)].

Improvements in acne lesions may be noticed after two weeks of RETIN-A MICRO therapy, but more than seven weeks of therapy may be needed for sustained benefit.

If RETIN-A MICRO was temporarily discontinued due to local adverse reactions, RETIN-A MICRO therapy may be resumed upon resolution of local adverse reactions.

3 DOSAGE FORMS AND STRENGTHS

Gel (white to very pale yellow and opaque):

- 0.04% (0.4 mg of tretinoin per gram)
- 0.06% (0.6 mg of tretinoin per gram)
- 0.08% (0.8 mg of tretinoin per gram)
- 0.1% (1 mg of tretinoin per gram).

4 CONTRAINDICATIONS

None.

5 WARNINGS AND PRECAUTIONS

5.1 Local Skin Irritation

RETIN-A MICRO can cause local skin irritation, including excessive dryness, redness, swelling, peeling, itching, blistering, burning, or stinging [see Adverse Reactions (6.1)]. Use of RETIN-A MICRO in greater than the recommended dosage (more frequent than once daily application or excessive application) will not result in more rapid or improved acne results and may result in marked redness, peeling, or discomfort.

Tretinoin has been reported to cause severe local skin irritation on eczematous skin.

Weather extremes, such as severe wind or cold, may increase the risk of skin irritation in patients using RETIN-A MICRO.

To reduce the risk of local skin irritation, instruct RETIN-A MICRO-treated patients to:

- Avoid use of RETIN-A MICRO in areas affected by eczema.
- Minimize or avoid use of RETIN-A MICRO with weather extremes.
- Wash the treated skin gently, using a mild, non-medicated soap, pat it dry, and avoid washing the treated skin too often or scrubbing it hard when washing. RETIN-A MICRO is not recommended with concomitant use of medicated or abrasive soaps and cleansers, products that have a strong drying effect, products with high concentrations of alcohol, astringents, spices, or lime peels.
- Apply a topical moisturizer.

Advise patients that concomitant use of topical over the counter (OTC) acne products containing benzoyl peroxide, sulfur, resorcinol, or salicylic acid with RETIN-A MICRO may increase the risk for local skin irritation including dryness, erythema, and peeling. Consider withholding the use of topical OTC acne products if signs of skin irritation develop. Advise patients to allow the skin irritation effects of the topical OTC acne products to subside before initiation of RETIN-A MICRO treatment.

If severe local skin irritation occurs, discontinue RETIN-A MICRO use temporarily or permanently.

Efficacy of RETIN-A MICRO at reduced frequencies of application has not been established.

5.2 Initial Worsening of Inflammatory Acne Vulgaris

During the early weeks of RETIN-A MICRO treatment, an apparent exacerbation of inflammatory acne vulgaris lesions may occur. If RETIN-A MICRO is tolerated, initial worsening of inflammatory acne vulgaris lesions should not be considered a reason to discontinue therapy.

5.3 Photosensitivity

RETIN-A MICRO can cause photosensitivity. Advise patients to avoid or minimize unnecessary exposure to ultraviolet (UV) light, including sunlight and sunlamps, while using RETIN-A MICRO. Advise patients with sunburn to not use RETIN-A MICRO until the sunburn fully recovers.

Advise patients, especially those who may be required to have extended periods of UV light exposure (e.g., due to occupation or sports), those with inherent sensitivity to the sun, or those using drugs that cause photosensitivity, to use sun protection daily in the form of sunscreen (sun protection factor [SPF] ≥ 15) and sun-protective clothing, when UV exposure cannot be avoided, even on days when it is not sunny or inside activities are expected.

6 ADVERSE REACTIONS

6.1 Clinical Trials Experience

Because clinical trials are conducted under widely varying conditions, adverse reaction rates observed in the clinical trials of a drug cannot be directly compared to rates in the clinical trials of another drug and may not reflect the rates observed in practice.

RETIN-A MICRO, 0.1%

The safety of RETIN-A MICRO, 0.1% for the treatment of acne vulgaris was evaluated in two multicenter, double-blind, randomized, vehicle-controlled clinical trials (Studies 1 and 2). A total of 347 subjects with acne vulgaris were treated in Studies 1 and 2 in which 172 subjects received RETIN-A MICRO, 0.1% and 175 subjects received vehicle, applied topically once daily in the evening, for 12 weeks. Mean age was 19 years (range 11-40) and 55% were female [see Clinical Studies (14.1)]. RETIN-A MICRO is not approved for use in pediatric patients younger than 12 years of age [see Indications and Usage (1)].

In Studies 1 and 2, subjects treated with RETIN-A MICRO, 0.1% had increased cutaneous irritation scores for erythema, peeling, dryness, burning/stinging, or itching that peaked during the initial two weeks of therapy and decreased thereafter, compared to those treated with vehicle [see Warnings and Precautions (5.1)]. During the 12-week treatment period, no more than 3% of RETIN-A MICRO, 0.1%-treated subjects had cutaneous irritation scores indicative of severe cutaneous irritation and 6% (14/224) of RETIN-A MICRO 0.1%-treated subjects discontinued treatment due to cutaneous irritation. Of these 14 subjects, four had severe cutaneous irritation after 3 to 5 days of treatment, with blistering in one subject.

RETIN-A MICRO, 0.04%

The safety of RETIN-A MICRO, 0.04% for the treatment of acne vulgaris was evaluated in two multicenter, double-blind, randomized, vehicle-controlled clinical trials (Studies 3 and 4). A total of 451 subjects with acne vulgaris were treated in Studies 3 and 4 in which 225 subjects received RETIN-A MICRO, 0.04% and 226 subjects received vehicle, applied once daily in the evening, for 12 weeks. Mean age was 19 years (range 11-49) and 57% were female [see Clinical Studies (14.2)]. RETIN-A MICRO is not approved for use in pediatric patients younger than 12 years of age [see Indications and Usage (1)].

In Studies 3 and 4, subjects treated with RETIN-A MICRO, 0.04% had increased cutaneous irritation scores for erythema, peeling, dryness, burning/stinging, or itching that peaked during the initial two weeks of therapy and decreased thereafter, compared to those treated with vehicle [see Warnings and Precautions (5.1)]. Approximately half of the 225 subjects in the RETIN-A MICRO, 0.04%-treated group had cutaneous irritation at Week 2. Of the subjects who experienced cutaneous irritation, most had signs or symptoms that were mild in severity (severity was ranked on a 4-point ordinal scale: 0=none, 1=mild, 2=moderate, and 3=severe). Less than 10% of RETIN-A MICRO, 0.04%-treated subjects experienced moderate cutaneous irritation, and none had severe cutaneous irritation at Week 2.

In Studies 3 and 4, during the 12-week treatment period, the majority of RETIN-A MICRO, 0.04%-treated subjects experienced cutaneous irritation (mild, moderate, or severe), of which, 1% (2/225) of subjects had cutaneous irritation scores indicative of a severe irritation and 1.3% (3/225) of subjects discontinued treatment due to cutaneous irritation, which included dryness in one subject and peeling and urticaria in another.

RETIN-A MICRO, 0.04% and 0.1%

In a double-blind trial, 156 subjects with acne vulgaris were treated for 12-weeks with RETIN-A MICRO 0.04% (n=78) or 0.1% (n=78) topically once daily. In this trial, the most frequently reported adverse events affected the skin and subcutaneous tissue (15% in the 0.04% group, and 21% in the 0.1% group). The most prevalent events in the 0.04% group were skin irritation (6%); and in the 0.1% group, skin burning (8%), erythema (5%), skin irritation (4%), and dermatitis (4%). In this trial, 63% of the adverse events were of mild intensity, and 34% were of moderate intensity.

6.2 Postmarketing Experience

The following adverse reactions have been identified during post-approval use of RETIN-A MICRO and other topical tretinoin products. Because these reactions are reported voluntarily from a population of uncertain size, it is not always possible to reliably estimate their frequency or establish a causal relationship to drug exposure:

- Hyper- or hypopigmentation has been reported with repeated application of tretinoin.

8 USE IN SPECIFIC POPULATIONS

8.1 Pregnancy

Risk Summary

Available data from published prospective observational studies and retrospective cohort studies over decades of use of topical tretinoin in pregnant women have not established a drug-associated risk of major birth defects, miscarriage, or adverse maternal or fetal outcomes (see Data).

In animal reproduction studies with pregnant rats, alterations in the vertebrae and ribs of offspring were observed with daily topical dosing of 0.1% tretinoin gel (microsponge) during organogenesis at 5 to 10 times the maximum recommended human dose (MRHD). In animal reproduction studies with pregnant rabbits, fetal malformations, such as domed head and hydrocephaly, were observed in the offspring with daily topical dosing of 0.1% tretinoin gel (microsponge) during organogenesis at 10 to 19 times the MRHD [see Data].

The background risk of major birth defects and miscarriage for the indicated population is unknown. All pregnancies have a background risk of birth defect, loss, or other adverse outcomes. In the US general population, the estimated background risk of major birth defects and miscarriage in clinically recognized pregnancies is 2% to 4%, and 15% to 20%, respectively.

Data

Human Data: Published data from prospective observational studies and retrospective cohort studies on the use of topical tretinoin products during pregnancy have not identified an association with topical tretinoin and major birth defects or miscarriage. The available studies have methodologic limitations, including potential misclassification of exposure, small sample size and in some cases, lack of physical exam by an expert in birth defects.

Animal Data: For purposes of comparison of the animal exposure to systemic human exposure, the MRHD applied topically is defined as 1 gram of Retin-A Micro (tretinoin) Gel microsphere, 0.1%, applied daily to a 60 kg person (0.017 mg tretinoin/kg body weight).

Pregnant rats were treated with 0.1% tretinoin gel (microsponge) at daily dermal doses of 0.2, 0.5, and 1 mg/kg/day tretinoin on gestation days 6-15. Alterations were seen in the vertebrae and ribs of the affected offsprings at 0.5 mg/kg/day tretinoin, 5 to 10 times the MRHD based on body surface area (BSA) comparison.

Pregnant rabbits were treated with 0.1% tretinoin gel (microsponge) at daily dermal doses of 0.2, 0.5, and 1 mg/kg/day tretinoin on gestation days 7-19. Doses were administered topically for 24 hours a day while wearing Elizabethan collars to prevent ingestion of the drug. Increased incidences of certain alterations, including domed head and hydrocephaly, typical of retinoid-induced fetal malformations in this species were observed at doses of 0.5 and 1 mg/kg/day. Similar malformations were not observed in the offspring at 0.2 mg/kg/day, 4 times the MRHD based on BSA comparison. In a second rabbit study, pregnant rabbits were treated with 0.1% tretinoin gel (microsponge) at daily dermal doses of 0.5 or 1 mg/kg/day tretinoin on gestation days 7-19. Doses were administered topically for six hours per day while pregnant rabbits were restrained in stocks to prevent ingestion. The offspring of pregnant rabbits exposed to 0.5 or 1 mg/kg/day tretinoin did not show any malformations at doses up to 19 times (1.0 mg/kg/day) the MRHD based on BSA comparison, but fetal resorptions were increased at 0.5 mg/kg (10 times the MRHD based on BSA comparison).

Malformations (shortened or kinked tail) were observed in the offspring of pregnant rats treated with topical tretinoin at doses greater than 1 mg/kg/day during the period of organogenesis (10 times the MRHD based on BSA comparison). Anomalies (humerus: short 13%, bent 6%, os parietal incompletely ossified 14%) have also been reported in offspring when 10 mg/kg/day was topically applied to pregnant rats during the period of organogenesis. Supernumerary ribs have been a consistent finding in newborn rats when dams were treated topically or orally with retinoids.

Oral administration of tretinoin during organogenesis has been shown to cause malformations in the offspring of rats, mice, rabbits, hamsters, and nonhuman primates. Fetal malformations and death were observed when tretinoin was orally administered to pregnant rats during organogenesis at doses greater than 1 mg/kg/day (10 times the MRHD based on BSA comparison). Fetal malformations were reported at doses of 10 mg/kg/day or greater when administered to pregnant cynomolgus monkeys, but none were observed at 5 mg/kg/day (95 times the MRHD based on BSA comparison), although increased skeletal variations were observed at all doses. Dose-dependent increases in embryolethality and abortion also were reported. Similar results have also been reported in pigtail macaques.

In peri- and postnatal development studies in rats with oral tretinoin, decreased survival of neonates and growth retardation were observed at doses in excess of 2 mg/kg/day (19 times the MRHD based on BSA comparison).

Oral tretinoin has been shown to be fetotoxic in rats when administered at doses 24 times the MRHD based on BSA comparison.

Topical tretinoin has been shown to be fetotoxic in rabbits when administered at doses 10 times the MRHD based on BSA comparison.

8.2 Lactation

Risk Summary

There are no data on the presence of tretinoin or its metabolites in human milk, the effects on the breastfed infant, or the effects on milk production. It is not known whether topical administration of tretinoin could result in sufficient systemic absorption to produce detectable quantities in human milk (see Clinical Considerations).

The developmental and health benefits of breastfeeding should be considered along with the mother’s clinical need for RETIN-A MICRO and any potential adverse effects on the breastfed infant from the RETIN-A MICRO or from the underlying maternal condition.

Clinical Considerations

To minimize potential exposure to the infant via human milk, during breastfeeding, use RETIN-A MICRO on the smallest area of skin with acne and for the shortest duration possible. Advise breastfeeding women not to apply RETIN-A MICRO directly to the nipple and areola to avoid direct infant exposure.

8.4 Pediatric Use

The safety and effectiveness of RETIN-A MICRO for topical application for the treatment of acne vulgaris have been established in pediatric patients aged 12 years and older [see Clinical Studies (14)]. The safety and effectiveness of RETIN-A MICRO have not been established in pediatric patients younger than 12 years of age.

8.5 Geriatric Use

Clinical trials of RETIN-A MICRO did not include sufficient numbers of subjects aged 65 and over to determine whether they responded differently from younger adult subjects. Acne vulgaris is largely a disease of pediatric and young adult patients. Clinical studies of RETIN-A MICRO did not include patients 65 years of age and older.

10 OVERDOSAGE

Oral ingestion of large amounts of RETIN-A MICRO may lead to the same adverse reactions as those associated with excessive oral intake of Vitamin A.

Consider contacting the Poison Help Line (1-800-222-1222) or a medical toxicologist for overdose recommendations.

11 DESCRIPTION

Chemically, tretinoin is all-trans-retinoic acid, also known as (all-E)-3,7-dimethyl-9-(2,6,6-trimethyl-1-cyclohexen-1-yl)-2,4,6,8-nonatetraenoic acid. Tretinoin is a retinoid and a metabolite of naturally occurring Vitamin A. Tretinoin has a molecular weight of 300.44, a molecular formula of C20H28O2 and the following chemical structure:

RETIN-A MICRO (tretinoin) gel is for topical use. Each gram of RETIN-A MICRO gel:

- 0.04%, contains 0.4 mg of tretinoin
- 0.06%, contains 0.6 mg of tretinoin
- 0.08%, contains 0.8 mg of tretinoin
- 0.1%, contains 1 mg of tretinoin

The formulation contains methyl methacrylate/glycol dimethacrylate crosspolymer (MICROSPONGE® System), propylene glycol dicaprylate/dicaprate and butylated hydroxytoluene. Other components consist of benzyl alcohol, butylated hydroxytoluene, carbomer 974P, cyclomethicone and dimethicone copolyol, disodium EDTA, glycerin, PPG-20 methyl glucose ether distearate, propylene glycol, purified water, sorbic acid, and trolamine.

12 CLINICAL PHARMACOLOGY

12.1 Mechanism of Action

Although tretinoin activates three members of the retinoic acid (RAR) nuclear receptors (RARα, RARβ, and RARγ) which may act to modify gene expression, subsequent protein synthesis, and epithelial cell growth and differentiation, it has not been established whether the clinical effects of tretinoin are mediated through activation of retinoic acid receptors and/or other mechanisms.

The exact mechanism of action of topical tretinoin for treatment of acne vulgaris is unknown. Current evidence suggests that topical tretinoin decreases cohesiveness of follicular epithelial cells with decreased microcomedone formation. Additionally, tretinoin stimulates mitotic activity and increased turnover of follicular epithelial cells causing extrusion of the comedones.

12.3 Pharmacokinetics

Absorption

Tretinoin is a metabolite of Vitamin A. Percutaneous absorption, as determined by the cumulative excretion of radiolabeled drug into urine and feces, was assessed in 44 healthy males and females after single and repeated daily tretinoin applications up to 28 days of 500 mg of a 0.1% tretinoin gel product. In this assessment, estimates of in vivo bioavailability, mean (SD) were 0.82 (0.11)% and 1.41 (0.54)%, for single and multiple daily topical applications, respectively. The plasma concentrations of tretinoin and its metabolites, 13-cis-retinoic acid, all-trans-4-oxo-retinoic acid, and 13-cis-4-oxo-retinoic acid, generally ranged from 1 to 3 ng/mL and were essentially unaltered after either single or multiple daily applications of RETIN-A MICRO, 0.1%, relative to baseline levels.

Clinical pharmacokinetic studies have not been performed with RETIN-A MICRO, 0.08%, 0.06% and 0.04%.

13 NONCLINICAL TOXICOLOGY

13.1 Carcinogenesis, Mutagenesis, Impairment of Fertility

Dermal carcinogenicity testing has not been performed with RETIN-A MICRO (tretinoin) gel microsphere, 0.04%, 0.06%, 0.08%, or 0.1%.

In a 91-week dermal study in which CD-1 mice were administered 0.017% and 0.035% formulations of tretinoin, cutaneous squamous cell carcinomas and papillomas in the treatment area were observed in some female mice. These concentrations are near the tretinoin concentration of the 0.04% and 0.1% clinical formulations. A dose-dependent incidence of liver tumors in male mice was observed at those same doses. The maximum systemic doses associated with the administered 0.017% and 0.035% formulations are 0.5 and 1 mg/kg/day tretinoin, respectively. These doses are two and four times the MRHD based on BSA comparison.

The biological significance of these findings is not clear because they occurred at doses that exceeded the dermal maximally tolerated dose of tretinoin and because they were within the background natural occurrence rate for these tumors in this strain of mice. There was no evidence of carcinogenic potential when 0.025 mg/kg/day of tretinoin was administered topically to mice (0.1 times the MRHD based on BSA comparison). Studies in hairless albino mice suggest that concurrent exposure to tretinoin may enhance the tumorigenic potential of carcinogenic doses of UVB and UVA light from a solar simulator. This effect has been confirmed in a later study in pigmented mice, and dark pigmentation did not overcome the enhancement of photocarcinogenesis by 0.05% tretinoin. Although the significance of these studies to humans is not clear, patients should minimize exposure to sunlight or artificial ultraviolet irradiation sources [see Warnings and Precautions (5.3)].

The genotoxic potential of tretinoin was evaluated in the Ames assay and an in vivo mouse micronucleus assay. Both tests were negative.

The components of the microspheres have shown potential for genetic toxicity and fetal malformation. EGDMA, a component of the excipient acrylates copolymer, was positive for induction of structural chromosomal aberrations in an in vitro chromosomal aberration assay in mammalian cells in the absence of metabolic activation, and negative for genetic toxicity in the Ames assay, and an in vivo mouse micronucleus assay.

In fertility studies in rats with oral tretinoin, the no-observable effect level was 2 mg/kg/day (19 times the MRHD based on BSA comparison).

14 CLINICAL STUDIES

14.1 Clinical Studies with RETIN-A MICRO, 0.1%

The efficacy of RETIN-A MICRO, 0.1 was evaluated in two double-blind, randomized, vehicle-controlled trials in adult and pediatric subjects 11 years of age and older with acne vulgaris (Studies 1 and 2). RETIN-A MICRO is not approved for use in pediatric patients younger than 12 years of age [see Indications and Usage (1)]. RETIN-A MICRO, 0.1%, applied topically once daily in the evening, was superior to vehicle gel, applied topically once daily, in reducing the acne lesion counts. The mean reduction in lesion counts from baseline after treatment for 12 weeks are shown in Table 1:

Table 1: Mean Percent Reduction in Lesion Counts in Subjects with Acne Vulgaris at Week 12 in Studies 1 and 2
 | Study 1 |  | Study 2
 | RETIN-A MICRO 0.1% (n=72) | Vehicle Gel (n=71) | RETIN-A MICRO 0.1% (n=72) | Vehicle Gel (n=67)
Non-inflammatory lesion counts | 49% | 22% | 32% | 3%
Inflammatory lesion counts | 37% | 18% | 29% | 24%
Total lesion counts | 45% | 23% | 32% | 16%

Efficacy was also assessed by the investigator’s global evaluation, which included categories of “excellent”, “good”, “fair”, “no change”, and “poor”. RETIN-A MICRO 0.1%, was significantly superior (p<0.001) to the vehicle in the investigator’s global evaluation of the clinical response:

- In Study #1, 35% of RETIN-A MICRO 0.1% -treated subjects achieved an “excellent” result, as compared to 11% of vehicle-treated subjects.
- In Study #2, 28% of RETIN-A MICRO 0.1%-treated subjects achieved an “excellent” result, as compared to 9% of vehicle-treated subjects.

14.2 Clinical Studies with RETIN-A MICRO, 0.04%

In two vehicle-controlled clinical trials in adult and pediatric subjects 11 years of age and older with acne vulgaris (Studies 3 and 4). RETIN-A MICRO is not approved for use in pediatric patients younger than 12 years of age [see Indications and Usage (1)]. RETIN-A MICRO, 0.04%, applied topically once daily in the evening, was more effective (p<0.05) than vehicle gel, applied topically once daily, in reducing the acne lesion counts. The mean reduction in lesion counts from baseline after treatment for 12 weeks are shown in Table 2:

Table 2: Mean Percent Reduction in Lesion Counts in Subjects with Acne Vulgaris at Week 12 in Studies 3 and 4

 | Study 3 |  | Study 4
 | RETIN-A MICRO 0.04% (n=108) | Vehicle Gel (n=111) | RETIN-A MICRO 0.04% (n=110) | Vehicle Gel (n=103)
Non-inflammatory lesion counts | 37% | -2%* | 29% | 14%
Inflammatory lesion counts | 44% | 13% | 41% | 30%
Total lesion counts | 40% | 8% | 35% | 20%

* -2% represents a mean percent increase of 2%

Efficacy was also assessed by the investigator’s global evaluation, which included categories of “excellent”, “good”, “fair”, “no change”, and “poor”. RETIN-A MICRO 0.04% was superior (p<0.05) to the vehicle in the investigator's global evaluation of the clinical response:

- In Study #3, 14% of RETIN-A MICRO 0.04%-treated subjects achieved an “excellent” result, as compared to 5% of vehicle-treated subjects.
- In Study #4, 19% of RETIN-A MICRO 0.04%-treated subjects achieved an “excellent” result, as compared to 9% of vehicle-treated subjects.

16 HOW SUPPLIED/STORAGE AND HANDLING

How Supplied

RETIN-A MICRO (tretinoin) gel is opaque and white to very pale yellow in color and is supplied as follows:

Strength | Amount of Tretinoin in One Gram of Gel | Quantity/Package Type | NDC
0.04% | 0.4 mg | 20 gram tube | 0187-5144-20
0.04% | 0.4 mg | 45 gram tube | 0187-5144-45
0.04% | 0.4 mg | 50 gram pump | 0187-5144-50
0.06% | 0.6 mg | 50 gram pump | 0187-5146-50
0.08% | 0.8 mg | 50 gram pump | 0187-5148-50
0.1% | 1 mg | 20 gram tube | 0187-5140-20
0.1% | 1 mg | 45 gram tube | 0187-5140-45
0.1% | 1 mg | 50 gram pump | 0187-5140-50

Storage and Handling

Store at 20° to 25°C (68° to 77°F); excursions permitted from 15° to 30°C (59° to 86°F) [see USP Controlled Room Temperature].

Store pump upright.

17 PATIENT COUNSELING INFORMATION

Advise the patient to read the FDA-approved patient labeling (Patient Information).

Administration

Instruct the patient to [see Dosage and Administration (2)]:

- Thoroughly cleanse treatment area(s) with a mild, non-medicated cleanser then pat the skin dry prior to application of RETIN-A MICRO.
- Avoid contact with eyes, mouth, paranal creases of nose, and mucous membranes when applying RETIN-A MICRO.
- Apply a thin layer of RETIN-MICRO to cover the affected area(s).

Local Skin Irritation:

Advise the patient that use of RETIN-A MICRO greater than the recommended dosage will not result in more rapid of improved acne results and may result in marked redness, peeling or discomfort [see Warnings and Precautions (5.1)].

To reduce the risk of local skin irritation, advise the patient to:

- Minimize or avoid use of RETIN-A MICRO during weather extremes, such as severe wind or cold.
- Wash the treated skin gently, using a mild, non-medicated soap, and pat it dry, and avoid washing the treated skin too often or scrubbing it hard when washing.
- Not use medicated or abrasive soaps and cleansers, products that have a strong drying effect, products with high concentrations of alcohol, astringents, spices, and lime peels while using RETIN-A MICRO.
- Apply a topical moisturizer when using RETIN-A MICRO.

Advise the patient that concomitant use of topical OTC acne products containing benzoyl peroxide, sulfur, resorcinol, or salicylic acid with RETIN-A MICRO may increase the risk of local skin irritation. Advise the patient to withhold the use of topical OTC acne products if signs of skin irritation develop. Advise the patient to allow the skin irritation effects of the topical OTC acne products to subside before initiation of RETIN-A MICRO [see Warning and Precautions (5.1)].

Photosensitivity

Advise the patient to avoid or minimize unnecessary exposure to ultraviolet (UV) light, including sunlight and sunlamps, while using RETIN-A MICRO.

Advise the patient to not use RETIN-A MICRO on sunburn skin.

Advise the patient to use sun protection in the form of sunscreen (SPF ≥15) and sun-protective clothing if UV exposure cannot be avoided [see Warnings and Precautions (5.3)].

Lactation

Advise the female patient to use RETIN-A MICRO on the smallest area of skin with acne vulgaris and for the shortest duration possible while breastfeeding. To avoid direct infant exposure, instruct the patient who is breastfeeding not to apply RETIN-A MICRO directly to the nipple and areola [see Use in Specific Populations (8.2)].

Distributed by:
Bausch Health US, LLC
Bridgewater, NJ 08807 USA

Manufactured by:
Bausch Health Companies Inc.
Laval, Quebec H7L 4A8, Canada

RETIN-A MICRO is a registered trademark of Bausch Health Companies Inc. or its affiliates.

MICROSPONGE is a registered trademark of AMCOL International Corporation. All other products/brand names and/or logos are trademarks of the respective owners.

© 2025 Bausch Health Companies Inc. or its affiliates

9454709

Patient Information

RETIN-A MICRO® (ret-in-A MY-kroe)

(tretinoin) gel

for topical use

Important information: RETIN-A MICRO is for use on skin (topical use) only. Keep RETIN-A MICRO away from your eyes, mouth, vagina, or the corners of your nose.

What is RETIN-A MICRO?

RETIN-A MICRO is a prescription medicine used on the skin (topical) to treat acne in adults and children 12 years of age and older. Acne is a condition in which the skin has blackheads, whiteheads, and other pimples.

It is not known if RETIN-A MICRO is safe and effective in children under 12 years of age.

Before using RETIN-A MICRO, tell your healthcare provider about all of your medical conditions, including if you:

- have a skin condition called eczema.
- have a sunburn. You should not use RETIN-A MICRO until your skin has healed.
- are pregnant or plan to become pregnant. It is not known if RETIN-A MICRO will harm your unborn baby.
- are breastfeeding or plan to breastfeed. It is not known if RETIN-A MICRO passes into your breast milk. If you breastfeed during treatment with RETIN-A MICRO, use RETIN-A MICRO on the smallest area of the skin with acne and for the shortest time possible. Do not apply RETIN-A MICRO directly to the nipple and areola to avoid contact with your baby.

Tell your healthcare provider about all of the medicines you take, including prescription and over-the-counter medicines, vitamins, and herbal supplements.

Especially tell your healthcare provider if you use any skin products that contain benzoyl peroxide, sulfur, resorcinol, or salicylic acid. Using these topical skin products may increase the irritation of your skin when used with RETIN-A MICRO.

How should I use RETIN-A MICRO?

- Use RETIN-A MICRO exactly as your healthcare provider tells you to use it.
- Before you apply RETIN-A MICRO, gently wash the affected skin area with a mild, non-medicated soap. Rinse and pat your skin dry.
- Apply a thin layer of RETIN-A MICRO to the affected area 1 time a day in the evening.
- Do not use more RETIN-A MICRO than you need to cover the affected area and do not apply RETIN-A MICRO more than 1 time a day. Using too much RETIN-A MICRO or using it too often will not give you faster or better results, and you may get skin redness, peeling, or discomfort.
- You may use moisturizers after applying RETIN-A MICRO.
- Early in your treatment, you may get new pimples. At this stage, it is important to continue using RETIN-A MICRO.
- Your acne may not get better right away. Improvement in your acne may be noticed after 2 weeks of RETIN-A MICRO treatment, but more than 7 weeks of treatment may be needed before you get the full benefit. Wash your hands after applying RETIN-A MICRO.
- RETIN-A MICRO taken by mouth in large amounts may lead to the same side effects as those seen with large amounts of Vitamin A taken by mouth. Call the Poison Help line at 1-800-222-1222 if RETIN-A MICRO is taken by mouth.

What should I avoid while using RETIN-A MICRO?

- You should avoid sunlamps, tanning beds, and ultraviolet light during treatment with RETIN-A MICRO.
- Minimize exposure to sunlight.
- If you have to be in the sunlight, are sensitive to sunlight, or are using medicine that cause sensitive to sunlight, use a sunscreen with sun protection factor (SPF) of 15 or more. Wear a wide-brimmed hat or other protective clothing to cover the treated areas, even on days when it is not sunny, or you are inside.
- Do not use RETIN-A MICRO on sunburn skin until your skin has healed.

What are the possible side effects of RETIN-A MICRO?

RETIN-A MICRO can cause serious side effects, including:

- Skin irritation. RETIN-A MICRO can cause skin dryness, redness, swelling, peeling, itching, blistering, burning, or stinging. If you develop these symptoms, your healthcare provider may temporarily stop or completely stop your treatment with RETIN-A MICRO.
To help reduce the risk of skin irritation with RETIN-A MICRO:
- Avoid use of RETIN-A MICRO in skin areas affected by eczema.
- Minimize or avoid use of RETIN-A MICRO with weather extremes, such as severe wind or cold.
- Avoid washing the treated skin too often or scrubbing it hard when washing. RETIN-A MICRO is not recommended with use of medicated or abrasive soaps and cleansers, products that have a strong drying effect, products with high amounts of alcohol, astringents, spices, or lime peels.
- Apply a topical moisturizer when using RETIN-A MICRO.
It is not known if RETIN-A MICRO is effective when used less than 1 time a day.
- Sensitivity to sunlight. See “What should I avoid while using RETIN-A MICRO?”

The most common side effects of RETIN-A MICRO include skin redness, pain, and itching.

Tell your healthcare provider if you have any side effect that bothers you or that does not go away.

These are not all of the possible side effects of RETIN-A MICRO.

Call your doctor for medical advice about side effects. You may report side effects to FDA at 1-800-FDA-1088.

How should I store RETIN-A MICRO?

- Store RETIN-A MICRO at room temperature between 68° to 77°F (20° to 25°C).
- Store RETIN-A MICRO pump upright.

Keep RETIN-A MICRO and all medicines out of the reach of children.

General information about the safe and effective use of RETIN-A MICRO.

Medicines are sometimes prescribed for purposes other than those listed in a Patient Information leaflet. Do not use RETIN-A MICRO for a condition for which it was not prescribed. Do not give RETIN-A MICRO to other people, even if they have the same symptoms that you have. It may harm them. You can ask your pharmacist or healthcare provider for information about RETIN-A- MICRO that is written for health professionals.

What are the ingredients of RETIN-A MICRO?

Active ingredient: tretinoin

Inactive ingredients: benzyl alcohol, butylated hydroxytoluene, carbomer 974P, cyclomethicone and dimethicone copolyol, disodium EDTA, glycerin, methyl methacrylate/glycol dimethacrylate crosspolymer, PPG-20 methyl glucose ether distearate, propylene glycol, propylene glycol dicaprylate/dicaprate, purified water, sorbic acid, and trolamine

Distributed by: Bausch Health US, LLC, Bridgewater, NJ 08807 USA

Manufactured by: Bausch Health Companies Inc., Laval, Quebec H7L 4A8, Canada

RETIN-A MICRO is a registered trademark of Bausch Health Companies Inc. or its affiliates.

Microsponge is a registered trademark of AMCOL International Corporation. All other products/brand names and/or logos are trademarks of the respective owners.

© 2025 Bausch Health Companies Inc. or its affiliates

For more information, call 1-800-321-4576.

This Patient Information has been approved by the U.S. Food and Drug Administration.

Revised: 09/2025

9454709

PRINCIPAL DISPLAY PANEL - 0.08% 50 g Carton

NDC 0187-5148-50

RETIN-A MICRO®
(tretinoin) Gel microsphere
0.08%

PUMP

For Topical Use Only
Rx Only

Ortho Dermatologics

NET WT. 50 g

9440608
20000365J

PRINCIPAL DISPLAY PANEL - 0.06% 50 g Carton

NDC 0187-5146-50

RETIN-A MICRO®
tretinoin Gel (microsphere)
0.06%

PUMP

For Topical Use Only
Rx only

Ortho Dermatologics

NET WT. 50 g

9581504
20001795E

PRINCIPAL DISPLAY PANEL - 0.04% 50 g Carton

NDC 0187-5144-50

RETIN-A MICRO®
tretinoin gel (microsphere)
0.04%

PUMP

For Topical Use Only
Rx Only

Ortho Dermatologics

Net Wt. 50g

9450907

PRINCIPAL DISPLAY PANEL - 0.1% 50 g Carton

NDC 0187-5140-50

RETIN-A MICRO®
tretinoin gel (microsphere)
0.1%

PUMP

For Topical Use Only
Rx Only

Ortho Dermatologics

Net Wt. 50g

9450707